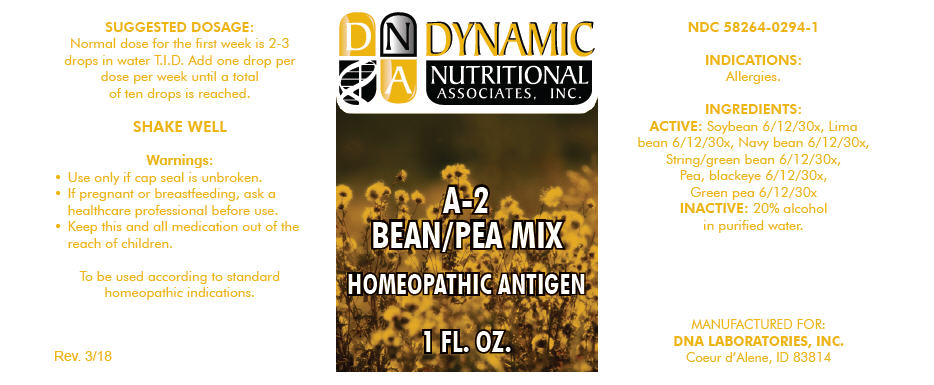 DRUG LABEL: A-2
NDC: 58264-0294 | Form: SOLUTION
Manufacturer: DNA Labs, Inc.
Category: homeopathic | Type: HUMAN OTC DRUG LABEL
Date: 20250109

ACTIVE INGREDIENTS: STRING BEAN 30 [hp_X]/1 mL; BLACK-EYED PEA 30 [hp_X]/1 mL; PEA 30 [hp_X]/1 mL; SOYBEAN 30 [hp_X]/1 mL; LIMA BEAN 30 [hp_X]/1 mL; KIDNEY BEAN 30 [hp_X]/1 mL
INACTIVE INGREDIENTS: ALCOHOL; WATER

A-2

NDC 58264-0294-1

INDICATIONS

PURPOSE

Allergies.

INGREDIENTS

ACTIVE

Soybean 6/12/30x, Lima bean 6/12/30x, Navy bean 6/12/30x, String/green bean 6/12/30x, Pea, blackeye 6/12/30x, Green pea 6/12/30x

INACTIVE

20% alcohol in purified water.

SUGGESTED DOSAGE

Normal dose for the first week is 2-3 drops in water T.I.D. Add one drop per dose per week until a total of ten drops is reached.

STORAGE AND HANDLING

SHAKE WELL

Warnings

- Use only if cap seal is unbroken.

PREGNANCY OR BREAST FEEDING

- If pregnant or breastfeeding, ask a healthcare professional before use.

KEEP OUT OF REACH OF CHILDREN

- Keep this and all medication out of the reach of children.

To be used according to standard homeopathic indications.

PRINCIPAL DISPLAY PANEL - 1 FL. OZ. Bottle Label

DYNAMIC
NUTRITIONAL
ASSOCIATES, INC.

A-2
BEAN/PEA MIX

HOMEOPATHIC ANTIGEN

1 FL. OZ.